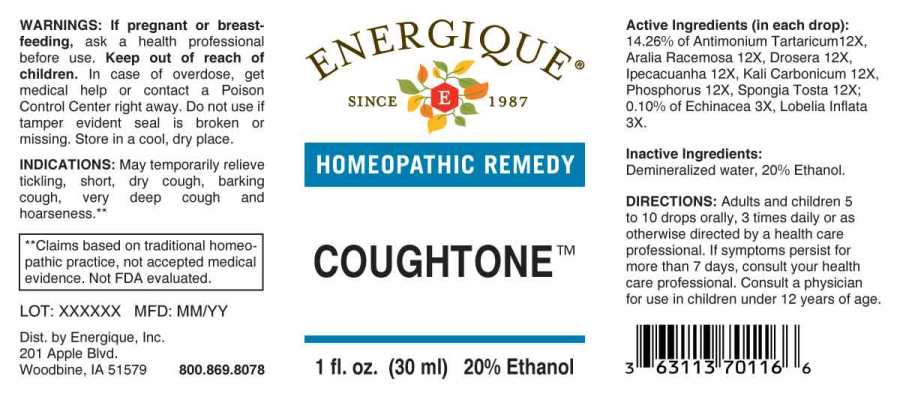 DRUG LABEL: COUGHTONE
NDC: 44911-0593 | Form: LIQUID
Manufacturer: Energique, Inc.
Category: homeopathic | Type: HUMAN OTC DRUG LABEL
Date: 20240123

ACTIVE INGREDIENTS: ECHINACEA ANGUSTIFOLIA WHOLE 3 [hp_X]/1 mL; LOBELIA INFLATA 3 [hp_X]/1 mL; ANTIMONY POTASSIUM TARTRATE 12 [hp_X]/1 mL; ARALIA RACEMOSA ROOT 12 [hp_X]/1 mL; DROSERA ROTUNDIFOLIA 12 [hp_X]/1 mL; IPECAC 12 [hp_X]/1 mL; POTASSIUM CARBONATE 12 [hp_X]/1 mL; PHOSPHORUS 12 [hp_X]/1 mL; SPONGIA OFFICINALIS SKELETON, ROASTED 12 [hp_X]/1 mL
INACTIVE INGREDIENTS: ALCOHOL; WATER

DRUG FACTS:

ACTIVE INGREDIENTS:

(in each drop): 14.26% of Antimonium Tartaricum 12X, Aralia Racemosa 12X, Drosera (Rotundifolia) 12X, Ipecacuanha 12X, Kali Carbonicum 12X, Phosphorus 12X, Spongia Tosta 12X; 0.10% of Echinacea (Angustifolia) 3X, Lobelia Inflata 3X.

INDICATIONS:

May temporarily relieve tickling, short, dry cough, barking cough, very deep cough and hoarseness.**

**Claims based on traditional homeopathic practice, not accepted medical evidence. Not FDA evaluated.

WARNINGS:

If pregnant or breast-feeding, ask a health professional before use.

Keep out of reach of children. In case of overdose, get medical help or contact a Poison Control Center right away.

Do not use if tamper evident seal is broken or missing.

Store in a cool, dry place.

DIRECTIONS:

Adults and children 5 to 10 drops orally, 3 times daily or as otherwise directed by a health care professional. If symptoms persist for more than 7 days, consult your health care professional. Consult a physician for use in children under 12 years of age.

INACTIVE INGREDIENTS:

Demineralized water, 20% Ethanol.

KEEP OUT OF REACH OF CHILDREN:

In case of overdose, get medical help or contact a Poison Control Center right away.

INDICATIONS:

May temporarily relieve tickling, short, dry cough, barking cough, very deep cough and hoarseness.**

**Claims based on traditional homeopathic practice, not accepted medical evidence. Not FDA evaluated.

QUESTIONS:

Dist. by Energique, Inc.

201 Apple Blvd

Woodbine, IA 51579 800.869.8078

PACKAGE LABEL DISPLAY:

ENERGIQUE

SINCE 1987

HOMEOPATHIC REMEDY

COUGHTONE

1 fl. oz. (30 ml)